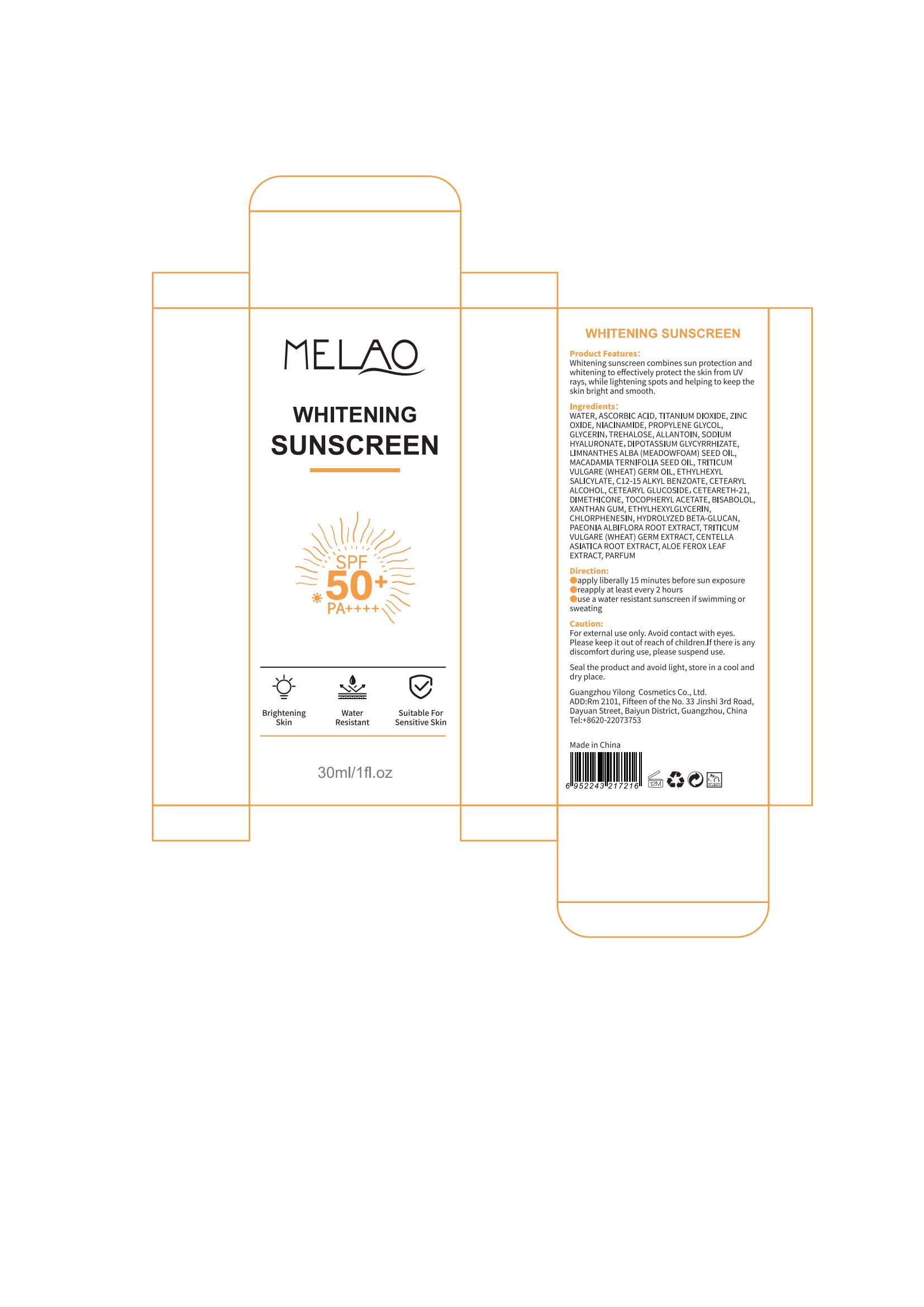 DRUG LABEL: MELAO WHITENING SUNSCREEN
NDC: 83566-288 | Form: CREAM
Manufacturer: Guangdong Aimu Biological Technology Co., Ltd
Category: otc | Type: HUMAN OTC DRUG LABEL
Date: 20250625

ACTIVE INGREDIENTS: ZINC OXIDE 6 g/100 g; ASCORBIC ACID 3 g/100 g; TITANIUM DIOXIDE 6 g/100 g
INACTIVE INGREDIENTS: GLYCERIN; LIMNANTHES ALBA WHOLE; NIACINAMIDE

MELAO WHITENING SUNSCREEN

Active ingredients

TITANIUM DIOXIDE 6%
ZINC OXIDE 6%

Purpose

sunscreen

Uses

apply liberally 15 minutes before sun exposure
reapply at least every 2 hours

Warnings

For external use only.

Stop use and ask a doctor if

rash occurs.

Do not use

on damaged or broken skin.

hen using this product

keep out of eyes. Rinse with water to remove.

Keep out of reach of children.

If swallowed, get medical help or contact a Poison Control Center right away.

Dosage

Squeeze out an appropriate amount of sunscreen and spread evenly on skin.

Inactive ingredients

WATER 34%
ASCORBIC ACID 3%
NIACINAMIDE 2%
PROPYLENE GLYCOL 5%
GLYCERIN 5%
TREHALOSE 1%
ALLANTOIN 0.3%
SODIUM HYALURONATE 0.2%
DIPOTASSIUM GLYCYRRHIZATE 0.5%
LIMNANTHES ALBA (MEADOWFOAM) SEED OIL 2%
MACADAMIA TERNIFOLIA SEED OIL 2%
TRITICUM VULGARE (WHEAT) GERM OIL 2%
ETHYLHEXYL SALICYLATE 3%
C12-15 ALKYL BENZOATE 3%
CETEARYL ALCOHOL 1%
CETEARYL GLUCOSIDE 2%
CETEARETH-21 1%
DIMETHICONE 1%
TOCOPHERYL ACETATE 2%
BISABOLOL 0.3%
XANTHAN GUM 0.4%
ETHYLHEXYLGLYCERIN 0.1%
CHLORPHENESIN 0.15%
HYDROLYZED BETA-GLUCAN 3%
PAEONIA ALBIFLORA ROOT EXTRACT 3%
TRITICUM VULGARE (WHEAT) GERM EXTRACT 2%
CENTELLA ASIATICA ROOT EXTRACT 2%
ALOE FEROX LEAF EXTRACT 2%
PARFUM 0.05